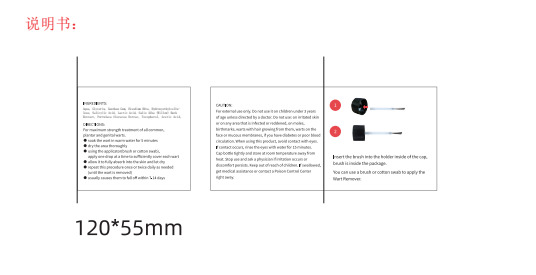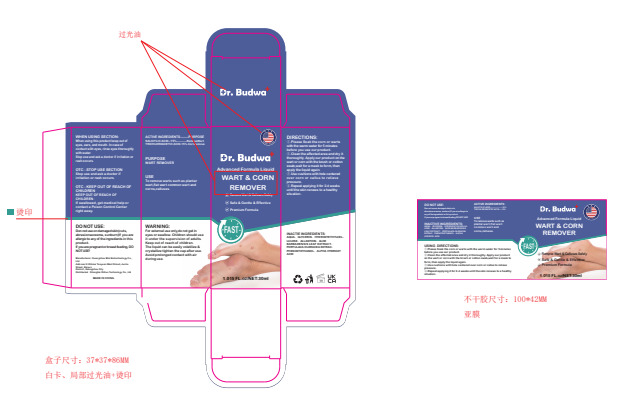 DRUG LABEL: Wart Remover Liquid
NDC: 84251-003 | Form: LIQUID
Manufacturer: Shanghai DiGuo Technology Co., Ltd
Category: otc | Type: HUMAN OTC DRUG LABEL
Date: 20240620

ACTIVE INGREDIENTS: SALICYLIC ACID 15 g/100 mL; TRICHLOROACETIC ACID 15 g/100 mL
INACTIVE INGREDIENTS: ALOE VERA LEAF; WATER; GLYCERIN; HYDROXYETHYL CELLULOSE, UNSPECIFIED; ALLANTOIN; PHENOXYETHANOL

84251-003

ACTIVE INGREDIENT

SALICYLIC ACID 15%

TRICHLOROACETIC ACID 15%

Purpose

WART REMOVER

Use

To remove warts such as plantar wart,flat wart common wart and corns,calluses.

Warnings

For extermal use only,do not get in eyes or swallow. Children should use it under the supervision of adults.

Keep out of reach of children. The liquid can be easily volatilize & crystallize tighten the cap after use. Awoid

prolonged contact with air during use.

Do not use

Don not use on damaged skin(cuts, abrasionseczema, sunburn)lf you are
allergic to any of the ingredients in this product. If you are pregnant or breast feeding,

DO NOTUSE!

When using this product keep out of eyes, ears, and mouth. In case of contact with eyes,

rinse eyes thoroughly with water. Stop use and ask a doctor if irritation or rash occurs.

Stop use and ask a doctor if irritation or rash occurs.

KEEP OUT OF REACH OF CHILDREN

If swallowed, get medical help or contact a Poison Control Center right away.

Directions

①.Please Soak the corn or warts with the warm water for 5 minutes before you use our product.
②.Clean the affected area and dry it thoroughly. Apply our product on the wart or corn with the brush or cotton
swab,wait for a mask to form, then apply the liquid again.
③.Use cushions with hole centered over corn or callus to relieve pressure.
④.Repeat applying it for 2-4 weeks until the skin renews to a healthy situation.

Inactive ingredients

AQUA、GLYCERIN. HYDROXYETHYLCEL. LULOSE、ALL ANTOIN. ALOE
BARBADENSIS LEAF EXTRACT. PORTUL ACA OLERACEA EXTRAC、
PHENOXYETHANOL、AL .PHA HYDROXY ACID

Other information

No data available